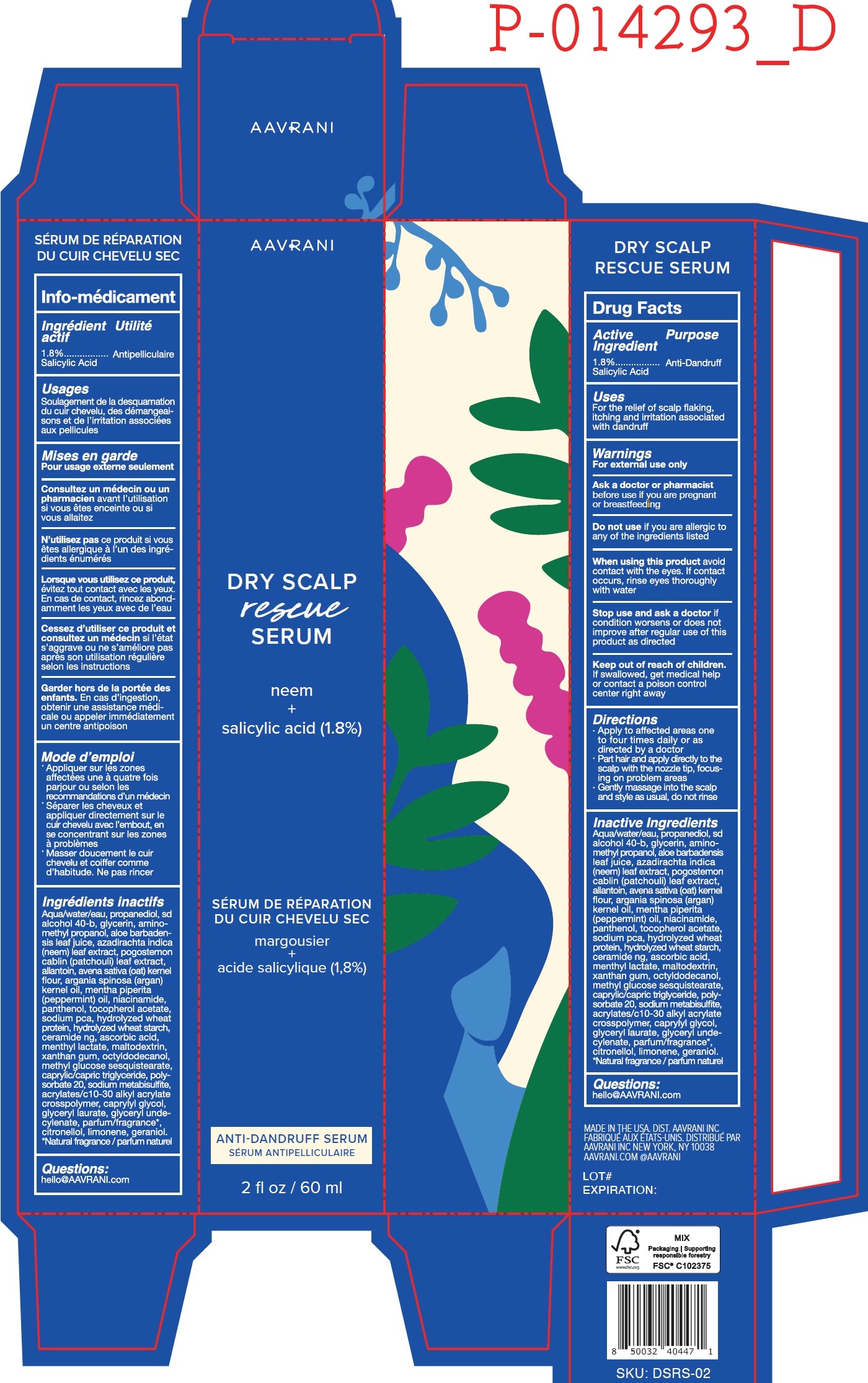 DRUG LABEL: AAVRANI DRY SCALP RESCUE SERUM
NDC: 83707-426 | Form: LIQUID
Manufacturer: AAVRANI, INC.
Category: otc | Type: HUMAN OTC DRUG LABEL
Date: 20231025

ACTIVE INGREDIENTS: SALICYLIC ACID 18 mg/1 mL
INACTIVE INGREDIENTS: WATER; PROPANEDIOL; GLYCERIN; AMINOMETHYLPROPANOL; ALOE VERA LEAF; AZADIRACHTA INDICA LEAF; POGOSTEMON CABLIN LEAF OIL; ALLANTOIN; OAT; ARGAN OIL; PEPPERMINT OIL; NIACINAMIDE; PANTHENOL; .ALPHA.-TOCOPHEROL ACETATE; SODIUM PYRROLIDONE CARBOXYLATE; CERAMIDE NG; ASCORBIC ACID; MENTHYL LACTATE, (-)-; MALTODEXTRIN; XANTHAN GUM; OCTYLDODECANOL; METHYL GLUCOSE SESQUISTEARATE; MEDIUM-CHAIN TRIGLYCERIDES; POLYSORBATE 20; SODIUM METABISULFITE; CAPRYLYL GLYCOL; GLYCERYL LAURATE; .BETA.-CITRONELLOL, (R)-; LIMONENE, (+)-; GERANIOL

AAVRANI DRY SCALP RESCUE SERUM

Active Ingredient

1.8% Salicylic Acid

Purpose

Anti-Dandruff

Uses

For the relief of scalp flaking, itching and irritation associated with dandruff

Warnings

For external use only

As a doctor or pharmacist

before use if you are pregnant or breastfeeding

Do not use

if you are allergic to any of the ingredients listed

When using this product

avoid contact with the eyes. If contact occurs, rinse eyes thoroughly with water

Stop use and ask a doctor if

condition worsens or does not improve after regular use of this product as directed

Keep out of reach of children.

If swallowed, get medical help or contact a poison control center right away.

Directions

- Apply to affected areas one to four times daily or as directed by a doctor
- Part hair and apply directly to the scalp with the nozzle tip, focusing on problem areas
- Gently massage into the scalp and style as usual, do not rinse

Inactive Ingredients

Aqua/water/eau, propanediol, sd alcohol 40-b, glycerin, aminomethyl propanol, aloe barbadensis leaf juice, azadirachta indica (neem) leaf extract, pogostemon cablin (patchouli) leaf extract, allantoin, avena sativa (oat) kernel flour, argania spinosa (argan) kernel oil, mentha piperita (peppermint) Oil, niacinamide, panthenol, tocopherol acetate, sodium pca, hydrolyzed wheat protein, hydrolyzed wheat starch, ceramide ng, ascorbic acid, menthyl lactate, maltodextrin, xanthan gum, octyldodecanol, methyl glucose sesquistearate, caprylic/capric triglyceride, polysorbate 20, sodium metabisulfite, acrylates/c 10-30 alkyl acrylate crosspolymer, caprylyl glycol, glyceryl laurate, glyceryl undecylenate, parfum/fragrance*, citronellol, limonene, geraniol.*Natural fragrance/parfum naturel

Questions:

hello@AAVRANI.com